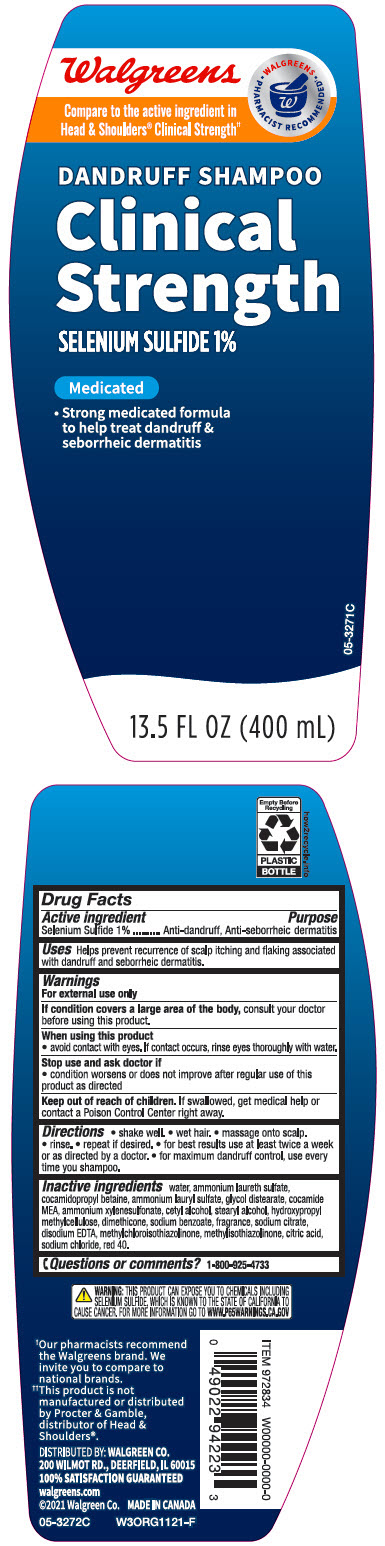 DRUG LABEL: Walgreens Clinical Strength Medicated Dandruff
NDC: 0363-9422 | Form: SHAMPOO
Manufacturer: Walgreen Company
Category: otc | Type: HUMAN OTC DRUG LABEL
Date: 20240509

ACTIVE INGREDIENTS: Selenium Sulfide 10 mg/1 mL
INACTIVE INGREDIENTS: Water; Ammonium Laureth-5 Sulfate; Cocamidopropyl Betaine; Ammonium Lauryl Sulfate; Glycol Distearate; COCO MONOETHANOLAMIDE; Ammonium Xylenesulfonate; Cetyl Alcohol; Stearyl Alcohol; Hypromellose, Unspecified; Dimethicone; Sodium Benzoate; SODIUM CITRATE, UNSPECIFIED FORM; EDETATE DISODIUM; Methylchloroisothiazolinone; Methylisothiazolinone; Citric Acid Monohydrate; Sodium Chloride; FD&C RED NO. 40

Walgreens Clinical Strength Medicated Dandruff Shampoo
Anti-dandruff, Anti-seborrheic dermatitis

Drug Facts

Active ingredient

Selenium Sulfide 1%

Purpose

Anti-dandruff, Anti-seborrheic dermatitis

Uses

Helps prevent recurrence of scalp itching and flaking associated with dandruff and seborrheic dermatitis.

Warnings

For external use only

If condition covers a large area of the body, consult your doctor before using this product.

When using this product

- avoid contact with the eyes. If contact occurs, rinse eyes thoroughly with water.

Stop use and ask a doctor if

- condition worsens or does not improve after regular use of this product as directed

Keep out of reach of children. If swallowed, get medical help or contact a Poison Control Center right away.

Directions

- shake well.
- wet hair.
- massage onto scalp.
- rinse.
- repeat if desired.
- for best results use at least twice a week or as directed by a doctor.
- for maximum dandruff control, use every time you shampoo.

Inactive ingredients

water, ammonium laureth sulfate, cocamidopropyl betaine, ammonium lauryl sulfate, glycol distearate, cocamide MEA, ammonium xylenesulfonate, cetyl alcohol, stearyl alcohol, hydroxypropyl methylcellulose, dimethicone, sodium benzoate, fragrance, sodium citrate, disodium EDTA, methylchloroisothiazolinone, methylisothiazolinone, citric acid, sodium chloride, red 40.

Questions or comments?

1-800-925-4733

DISTRIBUTED BY: WALGREEN CO.
200 WILMOT RD., DEERFIELD, IL 60015

PRINCIPAL DISPLAY PANEL - 400 mL Bottle Label

Walgreens

Compare to the active ingredient in
Head & Shoulders® Clinical Strength††

• WALGREENS •
PHARMACIST RECOMMENDED

DANDRUFF SHAMPOO

Clinical
Strength

SELENIUM SULFIDE 1%

Medicated

- Strong medicated formula
  to help treat dandruff &
  seborrheic dermatitis

05-3271C

13.5 FL OZ (400 mL)